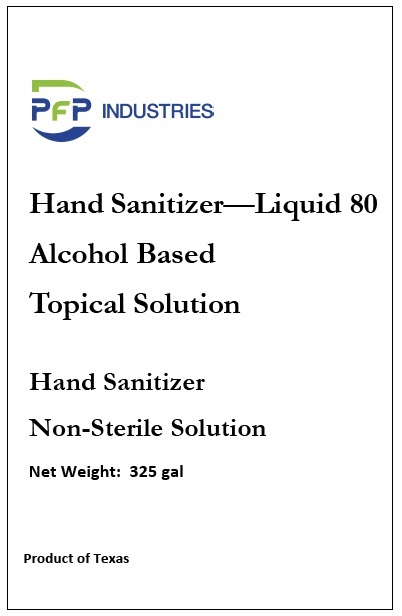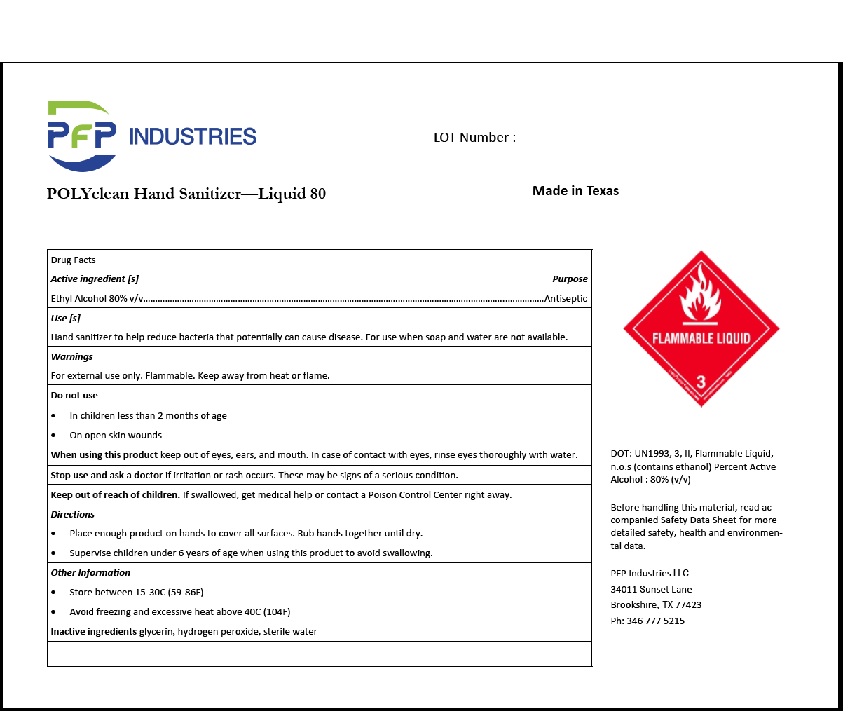 DRUG LABEL: PfP POLYclean Hand Sanitizer - Liq 80
NDC: 77034-001 | Form: LIQUID
Manufacturer: Pfp Industries, LLC (a Global Enterprise)
Category: otc | Type: HUMAN OTC DRUG LABEL
Date: 20200518

ACTIVE INGREDIENTS: ALCOHOL 80 L/100 L
INACTIVE INGREDIENTS: GLYCERIN; HYDROGEN PEROXIDE; WATER

PFPOLYclean Hand Sanitizer - Liquid 80

Drug Facts

Active ingredient [s]
Ethyl Alcohol 80%

Purpose
Antiseptic

INDICATIONS AND USAGE

Use [s]
Hand sanitizer to help reduce bacteria that potentially can cause disease. For use when soap and water are not available.

Warnings
For external use only. Flammable. Keep away from heat or flame.

Do not use
•In children less than 2 months of age
•On open skin wounds

When using this product keep out of eyes, ears, and mouth. In case of contact with eyes, rinse eyes thoroughly with water.

Stop use and ask a doctor if irritation or rash occurs. These may be signs of a serious condition.

Keep out of reach of children. If swallowed, get medical help or contact a Poison Control Center right away.

Directions
•Place enough product on hands to cover all surfaces. Rub hands together until dry.
•Supervise children under 6 years of age when using this product to avoid swallowing.

Other Information
•Store between 15-30C (59-86F)
•Avoid freezing and excessive heat above 40C (104F)

Inactive ingredients glycerin, hydrogen peroxide, sterile water

Product Labeling

PfP INDUSTRIES

Hand Sanitizer—Liquid 80

Alcohol Based

Topical Solution

Hand Sanitizer

Non-Sterile Solution

Net Weight: 325 gal

Product of Texas

PfP INDUSTRIES LOT Number :

POLYclean Hand Sanitizer—Liquid 80 Made in Texas

FLAMMABLE LIQUID

3

DOT: UN1993, 3, II, Flammable Liquid,

n.o.s (contains ethanol) Percent Active

Alcohol : 80% (v/v)

Before handling this material, read ac-

companied Safety Data Sheet for more

detailed safety, health and environmen-

tal data.

PFP Industries LLC

34011 Sunset Lane

Brookshire, TX 77423

Ph: 346 777 5215

res